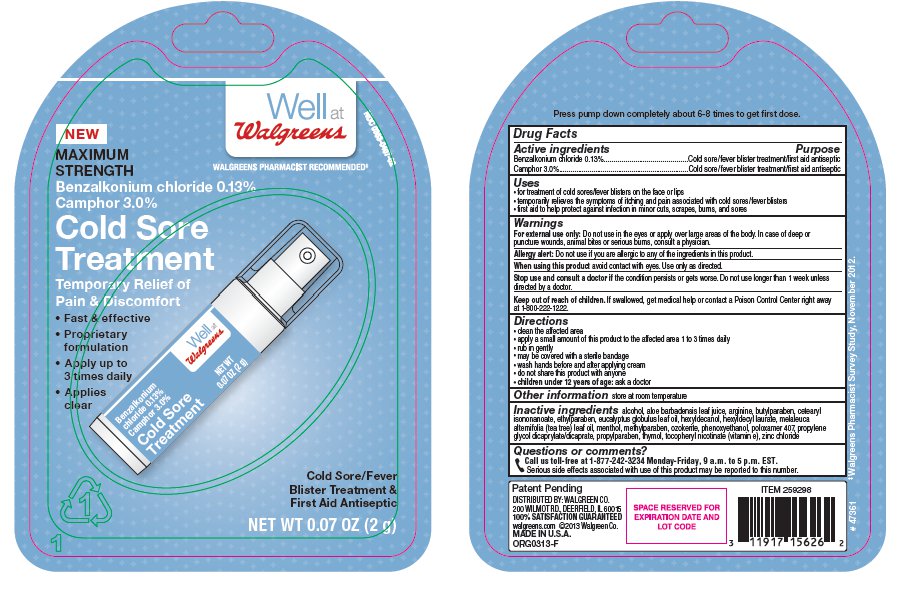 DRUG LABEL: Walgreens Cold Sore Treatment
NDC: 0363-0407 | Form: CREAM
Manufacturer: Walgreens
Category: otc | Type: HUMAN OTC DRUG LABEL
Date: 20130715

ACTIVE INGREDIENTS: Benzalkonium Chloride 1.3 mg/1 g; CAMPHOR (SYNTHETIC) 30 mg/1 g
INACTIVE INGREDIENTS: Alcohol; Aloe Vera Leaf; Arginine; Butylparaben; Ceresin; Cetearyl Isononanoate; Corymbia Citriodora Leaf Oil; Dipropylene Glycol Caprate/Caprylate Diester; Ethylparaben; Hexyldecanol; Hexyldecyl Laurate; Levomenthol; Methylparaben; PHENOXYETHANOL; Poloxamer 407; Propylparaben; Tea Tree Oil; Thymol; TOCOPHERYL NICOTINATE, D-.ALPHA.; Zinc Chloride

Drug Facts

Active Ingredient

Benzalkonium Chloride 0.13%

Camphor 3.0%

Purpose

Cold sore/fever blister treatment/first aid antiseptic

Uses

- for treatment of cold sores/fever blisters on the face or lips
- temporarily relieves the symptoms of itching and pain associated with cold sores/fever blisters
- first aid to help protect against infection in minor cuts, scrapes, burns, and sores

Warnings

For external use only: Do not use in the eyes or apply over large areas of the body. In case of deep or puncture wounds, animal bites or serious burns, consult a physician.

Allergy Alert: Do not use if you are allergic to any of the ingredients in this product.

When using this product avoid contact with eyes. Use only as directed.

Stop use and consult a doctor if the condition persists or gets worse. Do not use longer than 1 week unless directed by a doctor.

Keep out of reach of children. If swallowed, get medical help or contact a Poison Control Center right away at 1-800-222-1222

Directions

- clean the affected area
- apply a small amount of this product to the affected area 1 to 3 times daily
- rub in gently
- may be covered with a sterile bandage
- wash hands before and after applying cream
- do not share this product with anyone
- children under 12 years of age: ask a doctor

Other Information

store at room temperature

Inactive Ingredients

alcohol, aloe barbadensis leaf juice, arginine, butylparaben, cetearyl isononanoate, ethylparaben, eucalyptus globulus leaf oil, hexyl decyl laurate, hexyldecanole, melaleuca alternifolia (tea tree) leaf oil, menthol, methylparaben, ozokerite, phenoxyethanol, poloxamer 407, propylene glycol dicaprylate/dicaprate, propylparaben, thymol, tocopheryl nicotinate (vitamin e), zinc chloride

Questions or Comments?

Call us toll-free at 1-877-242-3234 Monday-Friday, 9 a.m. to 5 p.m. EST.
Serious side effects associated with use of this product may be reported to this number.